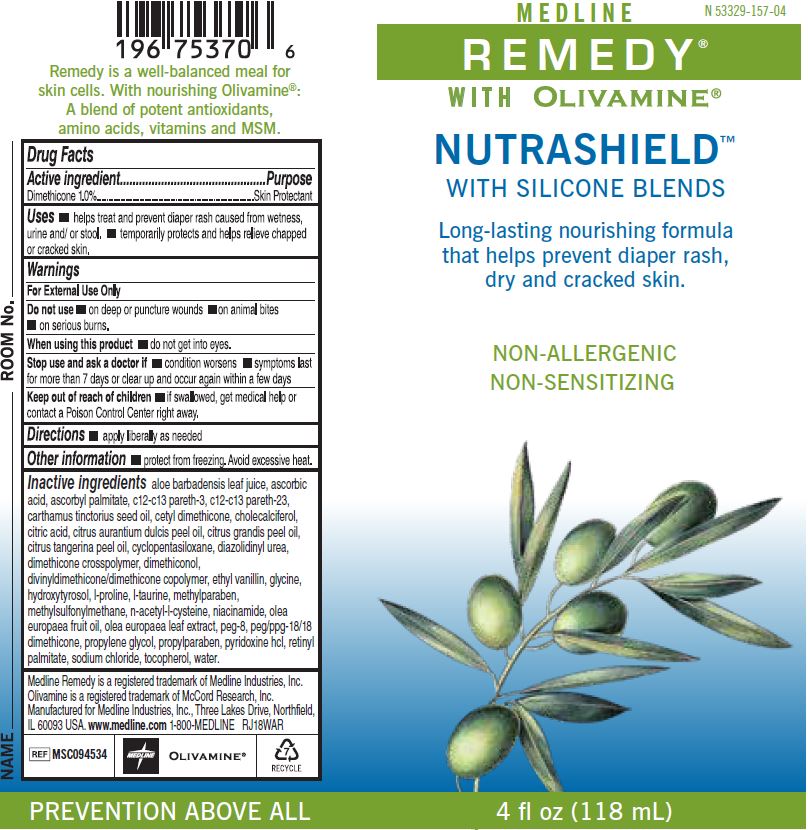 DRUG LABEL: Remedy Nutrashield
NDC: 53329-157 | Form: LOTION
Manufacturer: Medline Industries, LP
Category: otc | Type: HUMAN OTC DRUG LABEL
Date: 20251028

ACTIVE INGREDIENTS: DIMETHICONE 1 g/100 mL
INACTIVE INGREDIENTS: ALOE VERA LEAF; ASCORBIC ACID; ASCORBYL PALMITATE; SAFFLOWER OIL; CHOLECALCIFEROL; CITRIC ACID MONOHYDRATE; ORANGE OIL; CYCLOMETHICONE 5; DIAZOLIDINYL UREA; GLYCINE; METHYLPARABEN; DIMETHYL SULFONE; ACETYLCYSTEINE; NIACINAMIDE; OLIVE OIL; POLYETHYLENE GLYCOL 400; PROPYLENE GLYCOL; PROPYLPARABEN; PYRIDOXINE HYDROCHLORIDE; VITAMIN A PALMITATE; SODIUM CHLORIDE; .ALPHA.-TOCOPHEROL; VANILLIN; WATER; CORN OIL

157 Remedy Olivamine Nutrashield

Active ingredient

Dimethicone 1.0%

Purpose

Skin Protectant

Uses

- Helps treat and prevent diaper rash caused from wetness , urine, and/or stool.
- Temporarily protects and helps relieve chapped or cracked skin.

Warnings

For External Use Only.

Do not use

- on deep or puncture wounds
- on animal bites
- on serious burns

When using this product

- do not get into eyes

Stop use and ask a doctor if

- condition worsens
- symptoms last for more than 7 days or clear up and occur again within a few days

Keep out of reach of children.

If swallowed, get medical help or contact a Poison Control Center right away.

Directions

- Apply liberally as needed.

Other information

- Protect from freezing. Avoid excessive heat.

Inactive ingredients

aloe barbadensis leaf juice, ascorbic acid, ascorbyl palmitate, c12-c13 pareth-3, c12-c13 pareth-23, carthamus tinctorius seed oil, cetyl dimethicone, cholecalciferol, citric acid, citrus aurantium dulcis peel oil, citrus grandis peel oil, citrus tangerina peel oil, cyclopentasiloxane, diazolidinyl urea, dimethicone crosspolymer, dimethiconol,
divinyldimethicone/dimethicone copolymer, ethyl vanillin, glycine, hydroxytyrosol, l-proline, l-taurine, methylparaben, methylsulfonylmethane, n-acetyl-l-cysteine, niacinamide, olea europaea fruit oil, olea europaea leaf extract, peg-8, peg/ppg-18/18 dimethicone, propylene glycol, propylparaben, pyridoxine hcl, retinyl palmitate, sodium chloride, tocopherol, water.

Medline Remedy is a registered trademark of Medline Industries, Inc. Olivamine is a registered trademark of McCord Research, Inc. Manufactured for Medline Industries, Inc., Three Lakes Drive, Northfield, IL 60093 USA. www.medline.com 1-800-MEDLINE

REF MSC094534